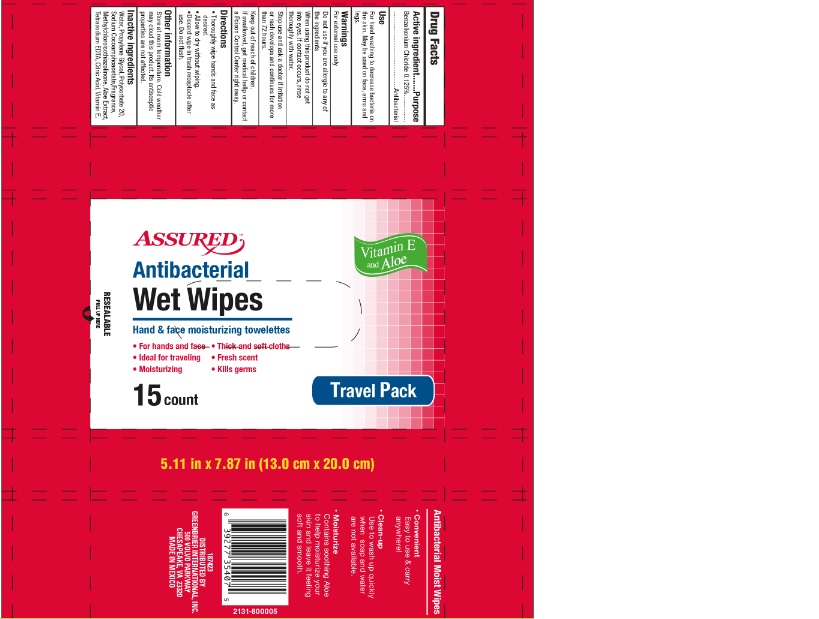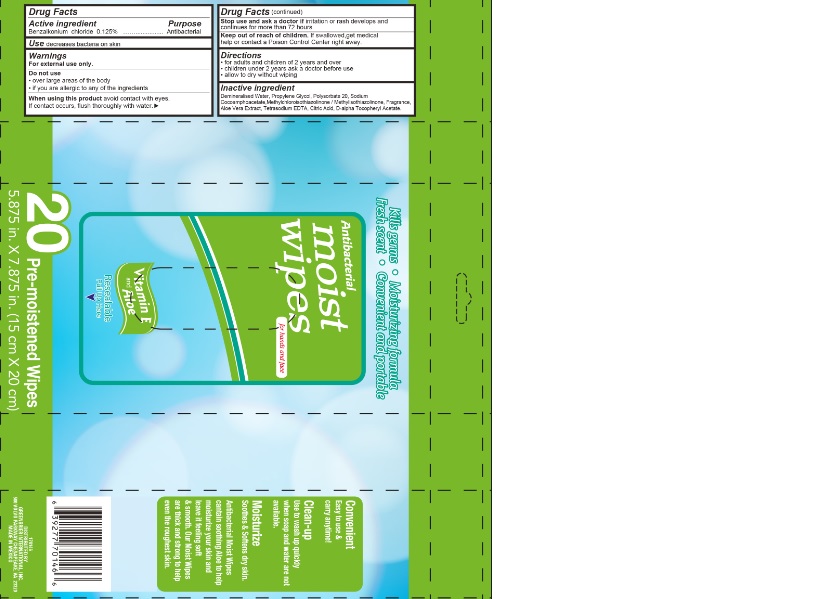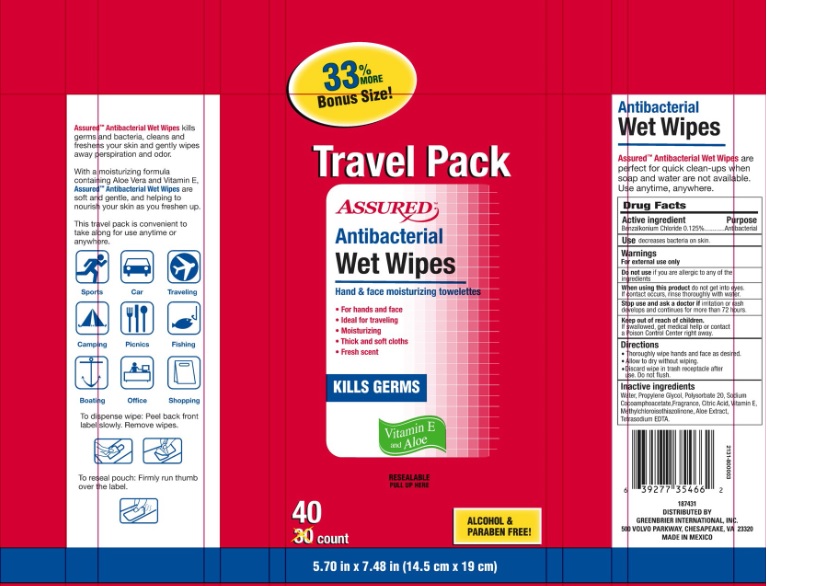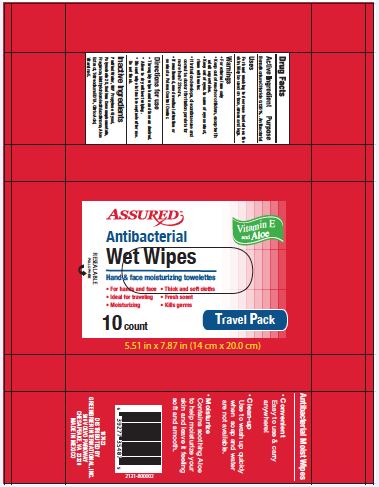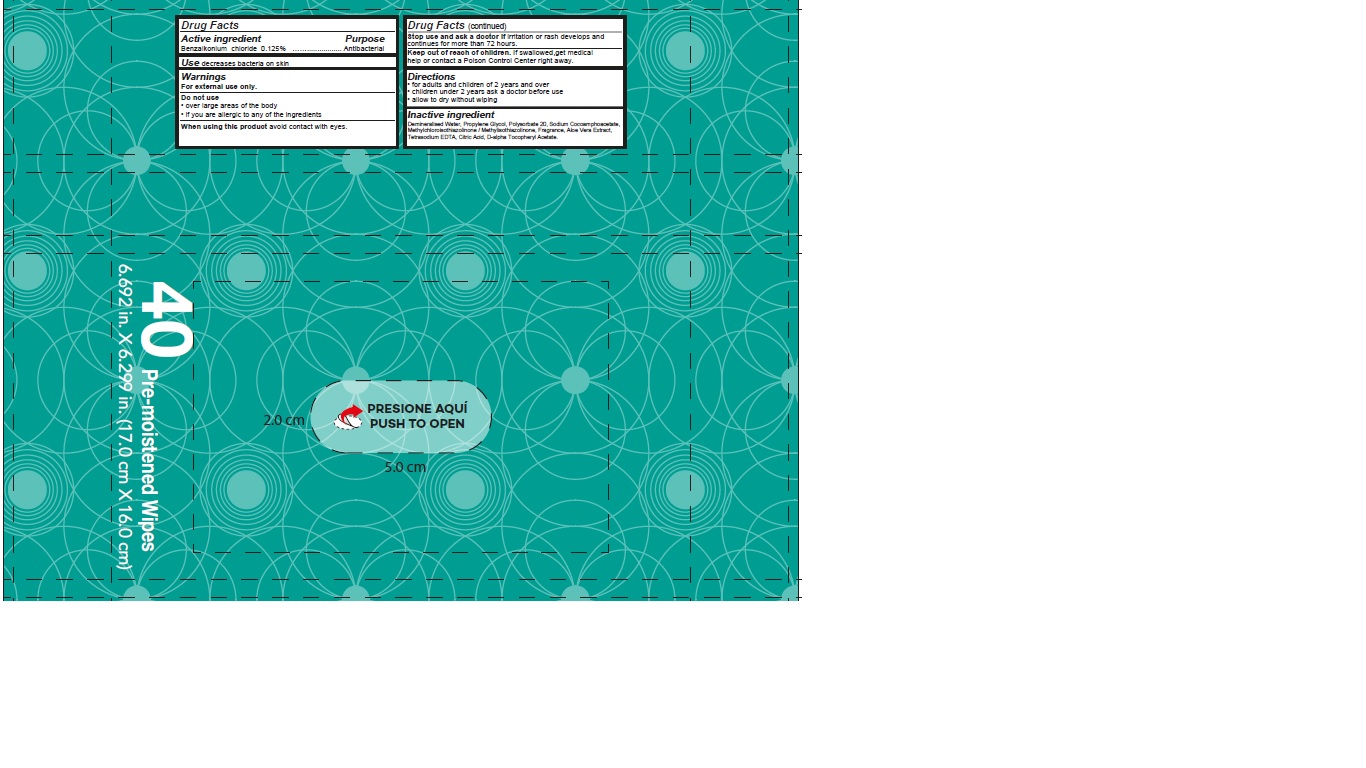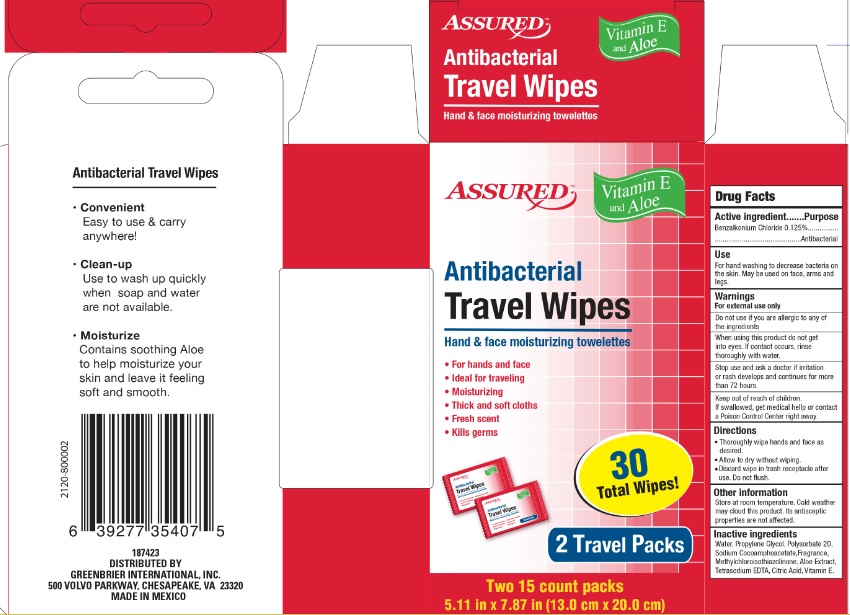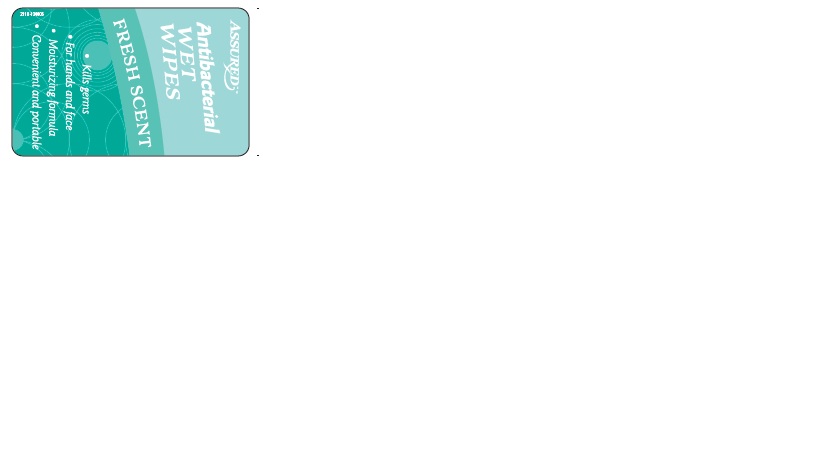 DRUG LABEL: ASSURED
NDC: 70697-800 | Form: SWAB
Manufacturer: INDELPA, S.A. DE C.V.
Category: otc | Type: HUMAN OTC DRUG LABEL
Date: 20220113

ACTIVE INGREDIENTS: BENZALKONIUM CHLORIDE 0.125 mg/100 mg
INACTIVE INGREDIENTS: WATER 98.54 mg/100 mg; ALOE VERA LEAF 0.05 mg/100 mg; POLYSORBATE 20 0.3 mg/100 mg; .ALPHA.-TOCOPHEROL ACETATE, DL- 0.01 mg/100 mg; PROPYLENE GLYCOL 0.5 mg/100 mg; SODIUM COCOAMPHOACETATE 0.2 mg/100 mg; METHYLCHLOROISOTHIAZOLINONE 0.1 mg/100 mg; EDETATE SODIUM 0.03 mg/100 mg; CITRIC ACID MONOHYDRATE 0.018 mg/100 mg

ACTIVE INGREDIENT

Benzalkonium Chloride 0.125%

PURPOSE

Antibacterial

USE

Decreases bacteria on skin.

WARNINGS

For external use only

DO NOT USE

If you are allergic to any of the ingredients

WHEN USING

Do not get into eyes.

If contact occurs, rinse thoroughly with water.

STOP USE

If irritation or rash develops and continues for more than 72 hours

ASK DOCTOR

If irritation or rash develops and continues for more than 72 hours

KEEP OUT OF REACH OF CHILDREN

If swallowed, get medical help or contact a Poison Control Center rigth away.

INDICATIONS AND USAGE

- Thoroughly wipe hands and face as desired.

- Allow to dry without wiping.
- Discard wipe in trash receptacle after use.
- Do not flush.

INSTRUCTIONS FOR USE

To dispense wipe: Peel back front label slowly. Remove wipes.

To reseal pouch: Firmly run thumb over the label.

STORAGE AND HANDLING

Store at room temperature. Cold weather may cloud this product. It's antiseptic properties are not affected.

INACTIVE INGREDIENT

Water, Propylene Glycol, Polysorbate 20, Sodium Cocoamphoacetate, Fragrance, Citric Acid, Vitamin E, Methylchloroisothiazolinone, Aloe Extract, Tetrasodium EDTA.

Dosage: Swab

Administration: Topical

SUMMARY OF SAFETY AND EFFECTIVENESS

AssuredTM Antibacterial Wet Wipes kills germs and bacteria, cleans and freshens your skin and gently wipes away perspiration and odor.

With moisturizing formula containing Aloe Vera and Vitamin E, AssuredTM Antibacterial Wet Wipes are soft and gentle, and helping to nourish your skin as you freshen up.

This travel pack is convenitent to take along for use anytime or anywhere.

ASSURED
Antibacterial
Wet Wipes
Hand & face moisturizing towelettes
For hands and face
Ideal for travling
Moisturizing
Thick and soft cloths
Fresh scent